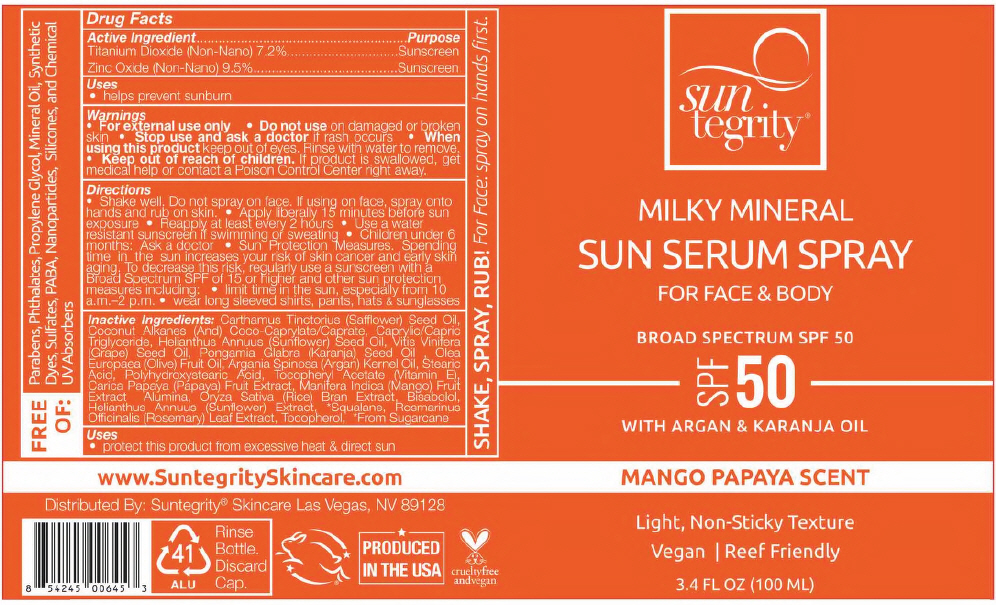 DRUG LABEL: MILKY MINERAL SUN SERUM
NDC: 69949-400 | Form: LOTION
Manufacturer: Synchronicity Spa, Inc. DBA Suntegrity
Category: otc | Type: HUMAN OTC DRUG LABEL
Date: 20241121

ACTIVE INGREDIENTS: TITANIUM DIOXIDE 72 mg/1 mL; ZINC OXIDE 95 mg/1 mL
INACTIVE INGREDIENTS: SAFFLOWER OIL; COCONUT ALKANES; COCOYL CAPRYLOCAPRATE; MEDIUM-CHAIN TRIGLYCERIDES; SUNFLOWER OIL; GRAPE SEED OIL; KARUM SEED OIL; OLIVE OIL; ARGAN OIL; STEARIC ACID; POLYHYDROXYSTEARIC ACID (2300 MW); .ALPHA.-TOCOPHEROL ACETATE; PAPAYA; MANGO; ALUMINUM OXIDE; RICE BRAN; LEVOMENOL; HELIANTHUS ANNUUS FLOWERING TOP; SQUALANE; ROSEMARY; TOCOPHEROL

MILKY MINERAL SUN SERUM SPRAY

Drug Facts

ACTIVE INGREDIENT

Active Ingredient | Purpose
Titanium Dioxide (Non-Nano) 7.2% | Sunscreen
Zinc Oxide (Non-Nano) 9.5% | Sunscreen

Uses

- helps prevent sunburn

Warnings

- For external use only

- Do not use on damaged or broken skin

- Stop use and ask a doctor if rash occurs

- When using this product keep out of eyes. Rinse with water to remove.

- Keep out of reach of children. If product is swallowed, get medical help or contact a Poison Control Center right away.

Directions

- Shake well. Do not spray on face. If using on face, spray onto hands and rub on skin.
- Apply liberally 15 minutes before sun exposure
- Reapply at least every 2 hours
- Use a water resistant sunscreen if swimming or sweating
- Children under 6 months: Ask a doctor
- Sun Protection Measures. Spending time in the sun increases your risk of skin cancer and early skin aging. To decrease this risk, regularly use a sunscreen with a Broad Spectrum SPF of 15 or higher and other sun protection measures including:
  - limit time in the sun, especially from 10 a.m.–2 p.m.
  - wear long sleeved shirts, pants, hats & sunglasses

Inactive Ingredients

Carthamus Tinctorius (Safflower) Seed Oil, Coconut Alkanes (And) Coco-Caprylate/Caprate, Caprylic/Capric Triglyceride, Helianthus Annuus (Sunflower) Seed Oil, Vitis Vinifera (Grape) Seed Oil, Pongamia Glabra (Karanja) Seed Oil , Olea Europaea (Olive) Fruit Oil, Argania Spinosa (Argan) Kernel Oil, Stearic Acid, Polyhydroxystearic Acid, Tocopheryl Acetate (Vitamin E), Carica Papaya (Papaya) Fruit Extract, Manifera Indica (Mango) Fruit Extract Alumina, Oryza Sativa (Rice) Bran Extract, Bisabolol, Helianthus Annuus (Sunflower) Extract, [From Sugarcane] Squalane, Rosmarinus Officinalis (Rosemary) Leaf Extract, Tocopherol,

Uses

- protect this product from excessive heat & direct sun

Distributed By: Suntegrity® Skincare Las Vegas, NV 89128

PRINCIPAL DISPLAY PANEL - 100 ML Bottle Label

sun
tegrity®

MILKY MINERAL

SUN SERUM SPRAY

FOR FACE & BODY

BROAD SPECTRUM SPF 50

SPF
50

WITH ARGAN & KARANJA OIL

MANGO PAPAYA SCENT

Light, Non-Sticky Texture

Vegan | Reef Friendly

3.4 FL OZ (100 ML)